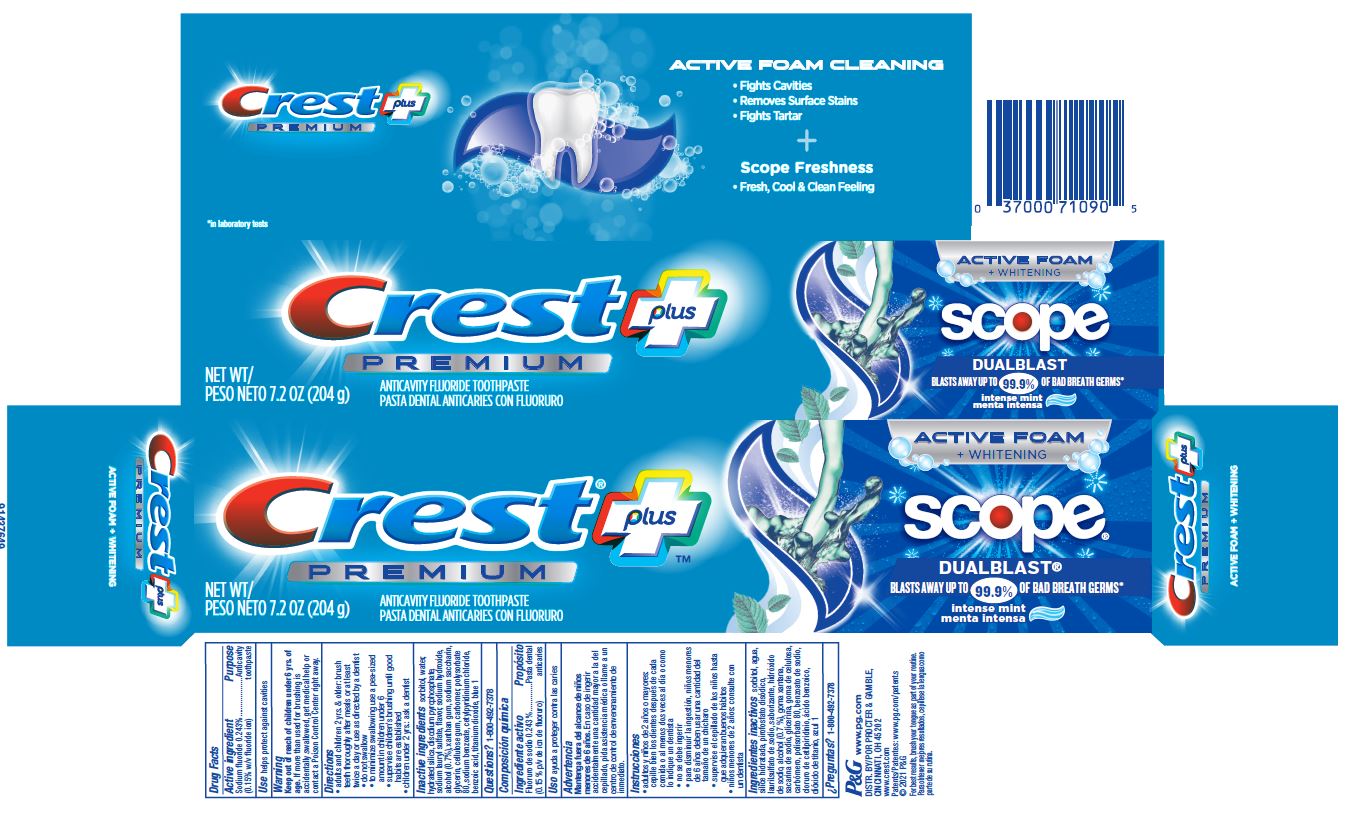 DRUG LABEL: Crest Premium Plus
NDC: 37000-990 | Form: PASTE, DENTIFRICE
Manufacturer: The Procter & Gamble Manufacturing Company
Category: otc | Type: HUMAN OTC DRUG LABEL
Date: 20250916

ACTIVE INGREDIENTS: SODIUM FLUORIDE 1.5 mg/1 g
INACTIVE INGREDIENTS: WATER; SORBITOL; HYDRATED SILICA; SODIUM LAURYL SULFATE; ALCOHOL; CARBOXYMETHYLCELLULOSE SODIUM; GLYCERIN; POLYSORBATE 80; SODIUM BENZOATE; CARBOXYPOLYMETHYLENE; CETYLPYRIDINIUM CHLORIDE; BENZOIC ACID; TITANIUM DIOXIDE; FD&C BLUE NO. 1; SODIUM ACID PYROPHOSPHATE; SODIUM HYDROXIDE; XANTHAN GUM; SACCHARIN SODIUM

Crest Premium Plus Scope Dual Blast Active Foam

Drug Facts

Active ingredient

Sodium fluoride 0.243%

(0.15% w/v fluoride ion)

Purpose

Anticavity toothpaste

Use

helps protect against cavities

Warnings

Keep out of reach of children under 6 yrs. of age. If more than used for brushing is accidentally swallowed, get medical help or contact a Poison Control Center right away.

Directions

- adults and children 2 yrs. & older: brush teeth thoroughly after meals or at least twice a day or use as directed by a dentist
- do not swallow
- to minimize swallowing use a pea-sized amount in children under 6
- supervise children's brushing until good habits are established
- children under 2 yrs.: ask a dentist

Inactive ingredients

sorbitol, water, hydrated silica, disodium pyrophosphate, sodium lauryl sulfate, flavor, sodium hydroxide, alcohol (0.7%), xanthan gum, sodium saccharin, glycerin, cellulose gum, carbomer, polysorbate 80, sodium benzoate, cetylpyridinium chloride, benzoic acid, titanium dioxide, blue 1

Questions?

1-800-492-7378

Dist. by Procter & Gamble,Cincinnati, OH 45202

PRINCIPAL DISPLAY PANEL - 204 g Tube Carton

Crest

plus

PREMIUM

NET WT/PESO NETO 7.2OZ (204 g)

ANTICAVITY FLUORIDE TOOTHPASTE

PASTA DENTAL ANTICARIES CON FLUORURO

ACTIVE FOAM

+WHITENING
scope®
DUALBLAST®

BLASTS AWAY 99.9% OF BAD BREATH GERMS*

intense mint

menta intensa